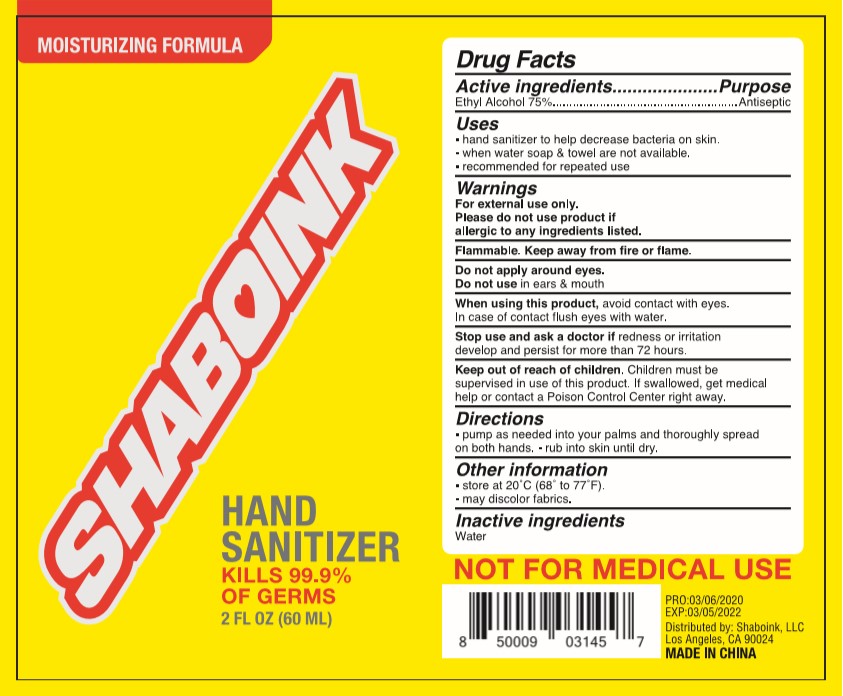 DRUG LABEL: SHABOINK
NDC: 75742-005 | Form: SPRAY
Manufacturer: Zhejiang Guoyao Jingyue Aerosol Co., Ltd.
Category: otc | Type: HUMAN OTC DRUG LABEL
Date: 20260105

ACTIVE INGREDIENTS: ALCOHOL 75 mL/100 mL
INACTIVE INGREDIENTS: WATER

Active Ingredients

Ethyl Alcohol 75%

Purpose

Antiseptic

Warnings

For external use only.

Please do not use product if allergic to any ingredients listed.

Flammable. Keep away from fire or flame.

Do not apply around eyes.

Do not use in ears & mouth

When using this product, avoid contact with eyes. In case of contact flush eyes with water.

Stop use and ask a doctor if redness or irritation develop and persist for more than 72 hours.

Keep out of reach of children

Children must be supervised in use of this product. If swallowed, get medical help or contact a Posion Control Center right away.

Uses

- hand snitizer to help decrease bacteria on skin.
- when water soap & towel are not available.
- recommended for repeated use

Directions

- pump as needed into your palms and thoroughly spread on both hands
- rub into skin until dry

Inactive ingredients

Water

Other information

- store at 20C(68 to 77F)
- may discolor fabrics.